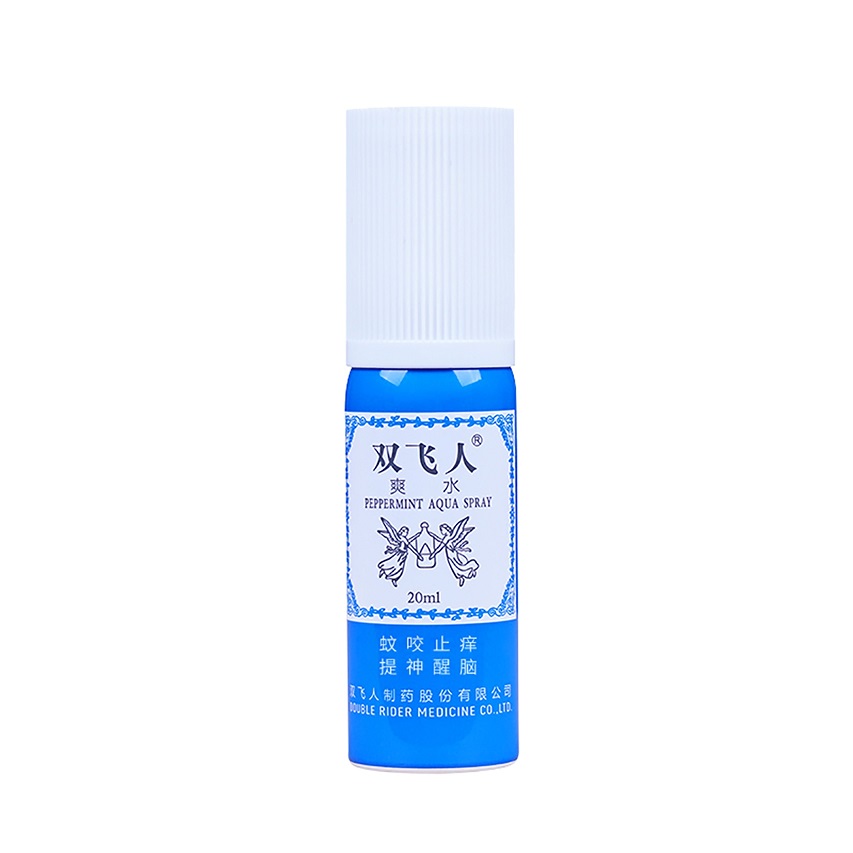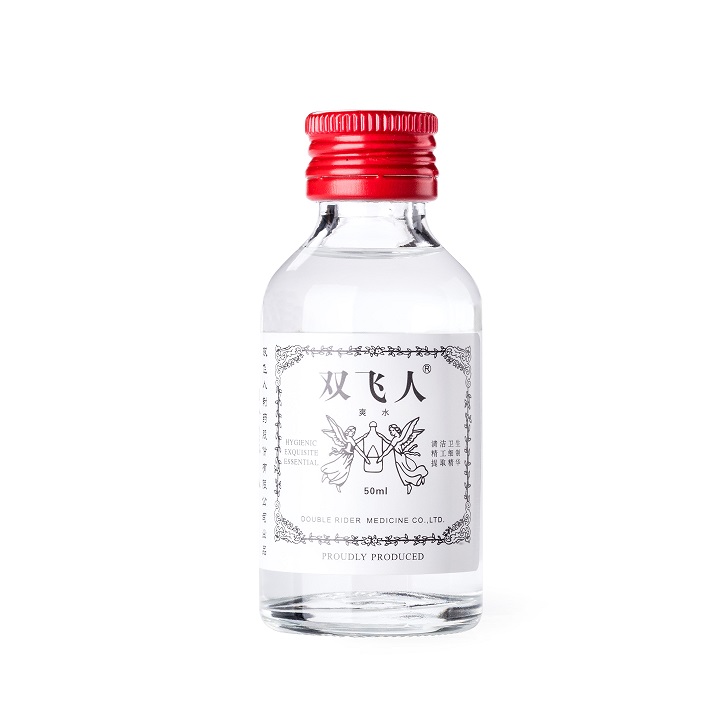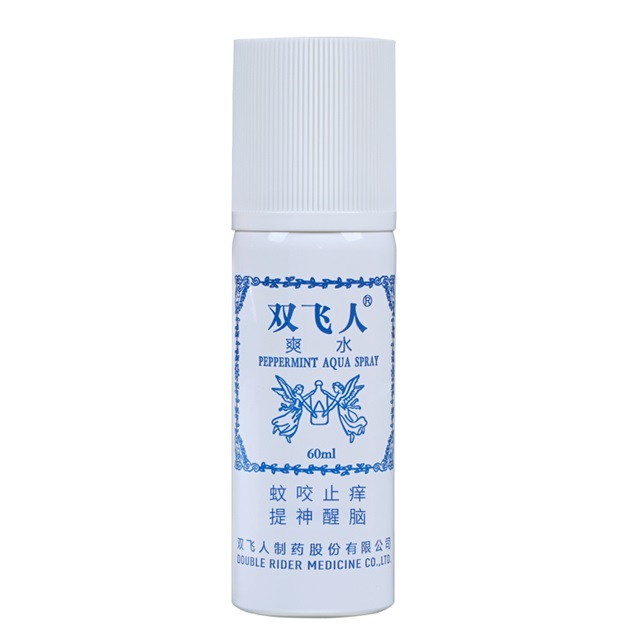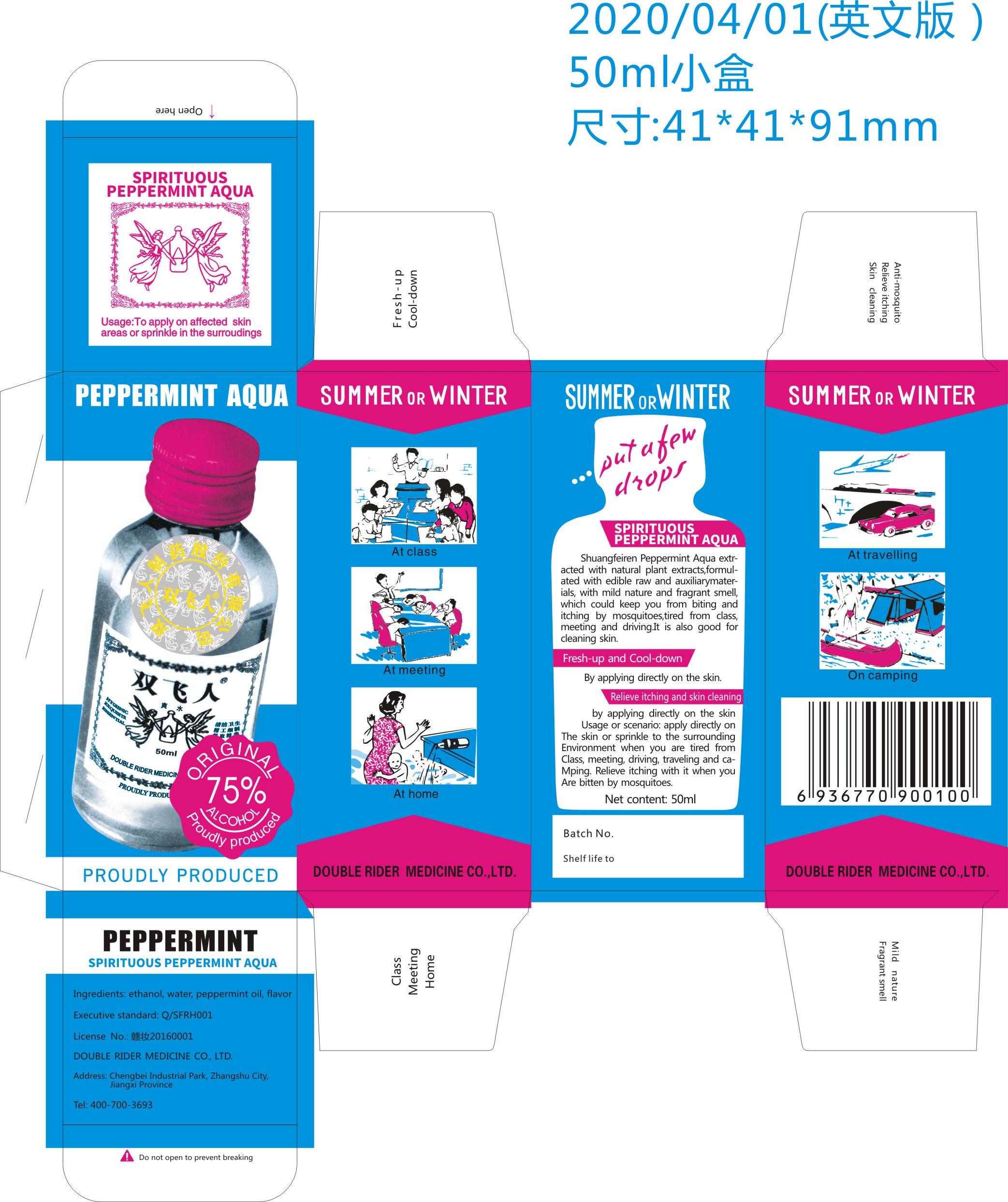 DRUG LABEL: Peppermint Aqua
NDC: 76845-101 | Form: LIQUID
Manufacturer: Double Rider Medicine Co., Ltd.
Category: otc | Type: HUMAN OTC DRUG LABEL
Date: 20200426

ACTIVE INGREDIENTS: ALCOHOL 75 mL/100 mL
INACTIVE INGREDIENTS: MENTHA ARVENSIS LEAF OIL; WATER

Peppermint Aqua

Peppermint Aqua

Active Ingredient(s)

Alcohol 75% v/v. Purpose: Antiseptic, Fresh-up and Cool-down

Purpose

Shuangfeiren Peppermint Aqua

Used for: refreshing, cooling, cleaning, anti-mosquito, relieve itching, class, meeting, traveling, camping, home.

mild nature, fragrant smell

Use

Apply directly on the skin or sprinkle to the surrounding environment.

Fresh-up with it when you are tired from class, meeting, driving, traveling and camping. Relieve itching with it when you are bitten by mosquitoes.

Warnings

For external use only. Flammable. Keep away from heat or flame

Do not use

- in children less than 2 months of age
- on open skin wounds

When using this product keep out of eyes, ears, and mouth. In case of contact with eyes, rinse eyes thoroughly with water.
Stop use and ask a doctor if irritation or rash occurs. These may be signs of a serious condition.
Keep out of reach of children. If swallowed, get medical help or contact a Poison Control Center right away.

Stop use and ask a doctor if irritation or rash occurs. These may be signs of a serious condition.

Keep out of reach of children. If swallowed, get medical help or contact a Poison Control Center right away.

Directions

- Take a few drops. Apply directly on the skin or sprinkle to the surrounding environment when you are tired from class, meeting, driving, traveling and camping. Relieve itching with it when you are bitten by mosquitoes.
- Supervise children under 6 years of age when using this product to avoid swallowing.

Other information

- Store between 15-30C (59-86F)
- Avoid freezing and excessive heat above 40C (104F)

Inactive ingredients

AQUA
MENTHA HAPLOCALYX OIL